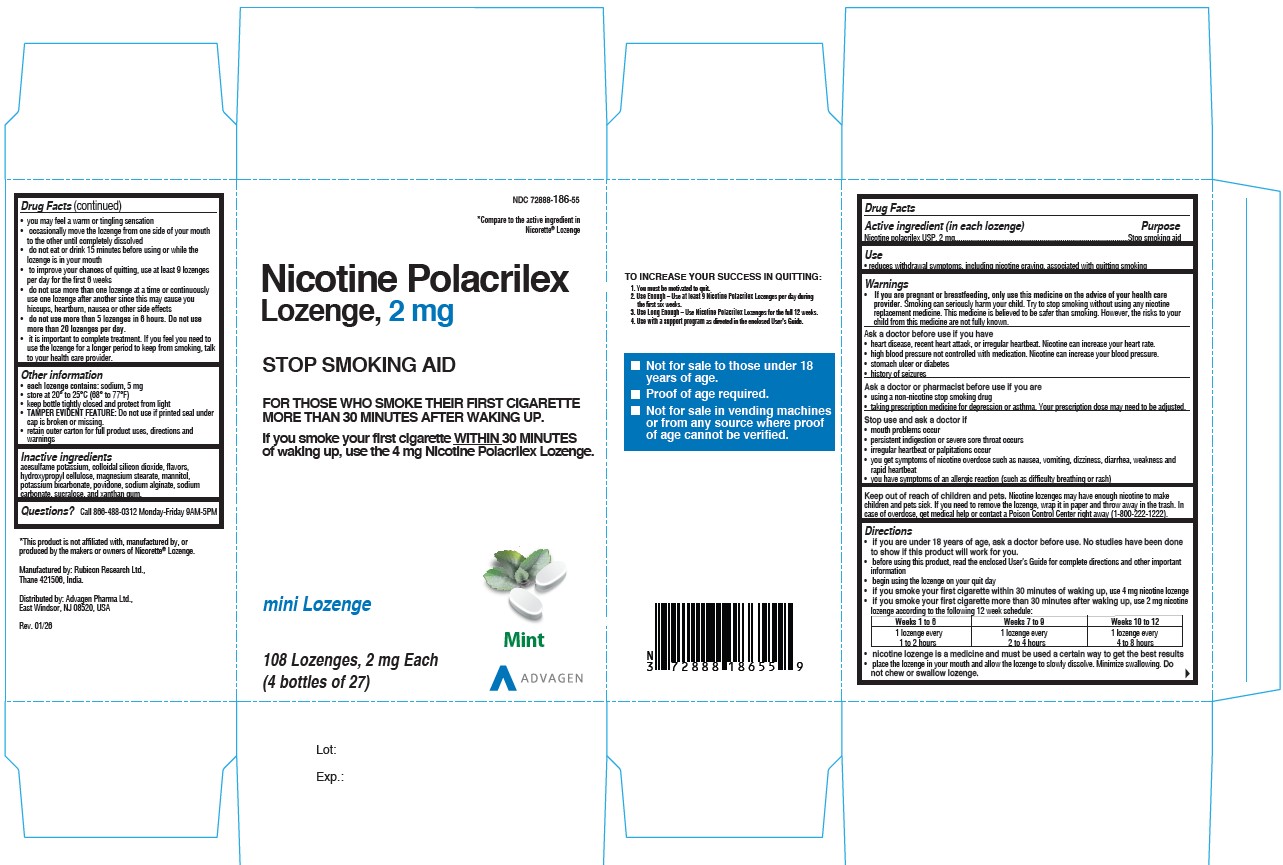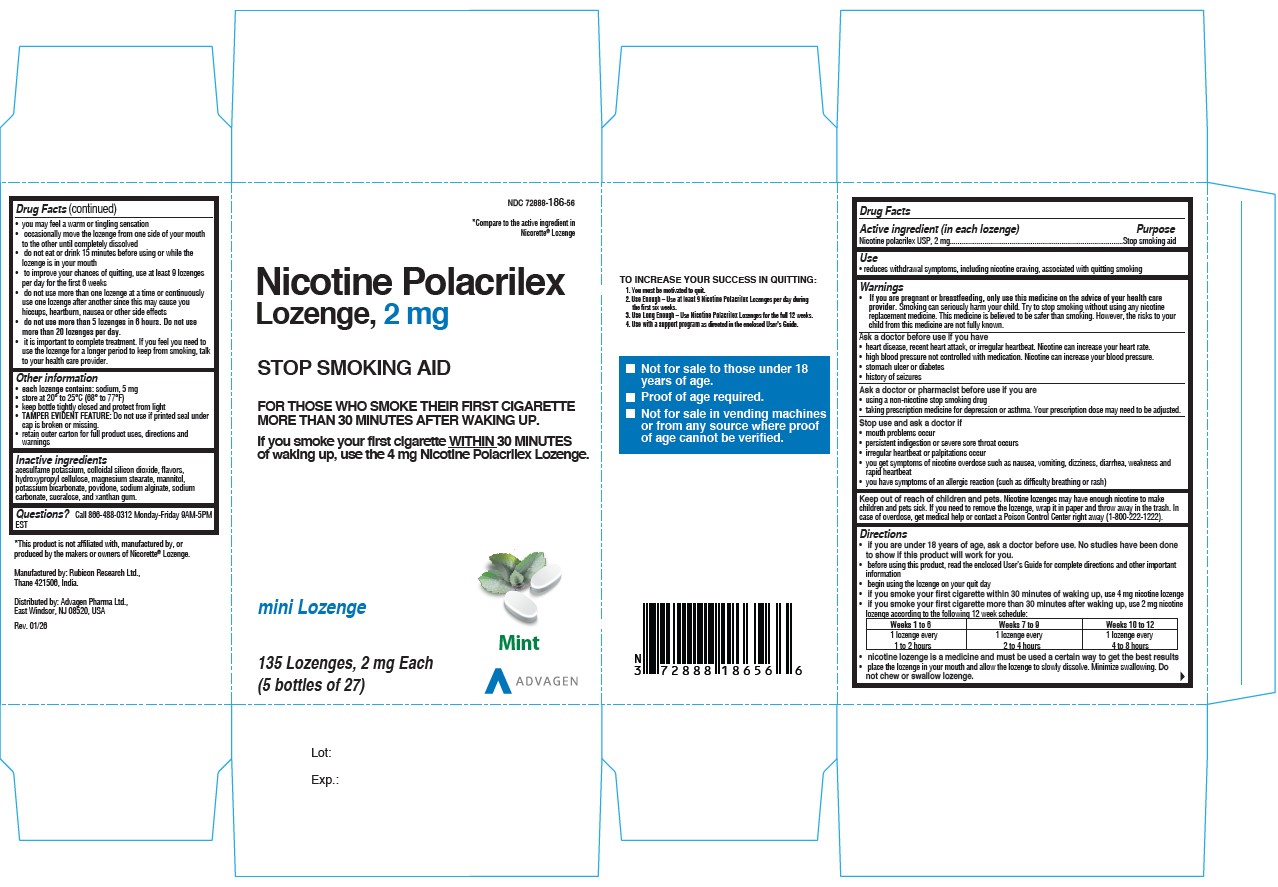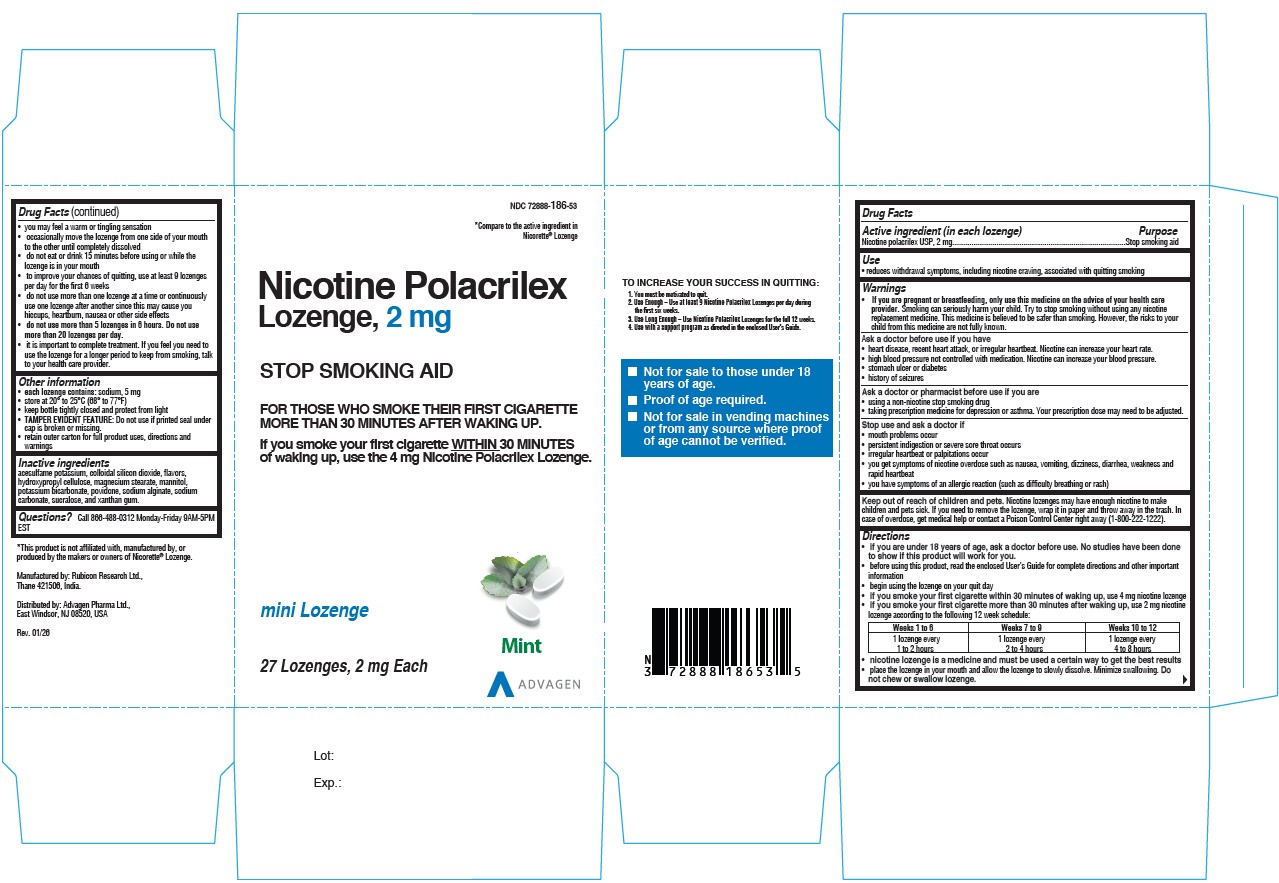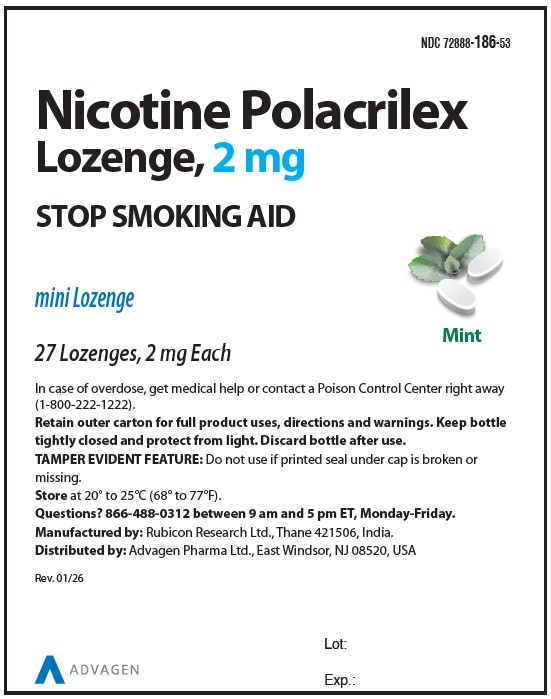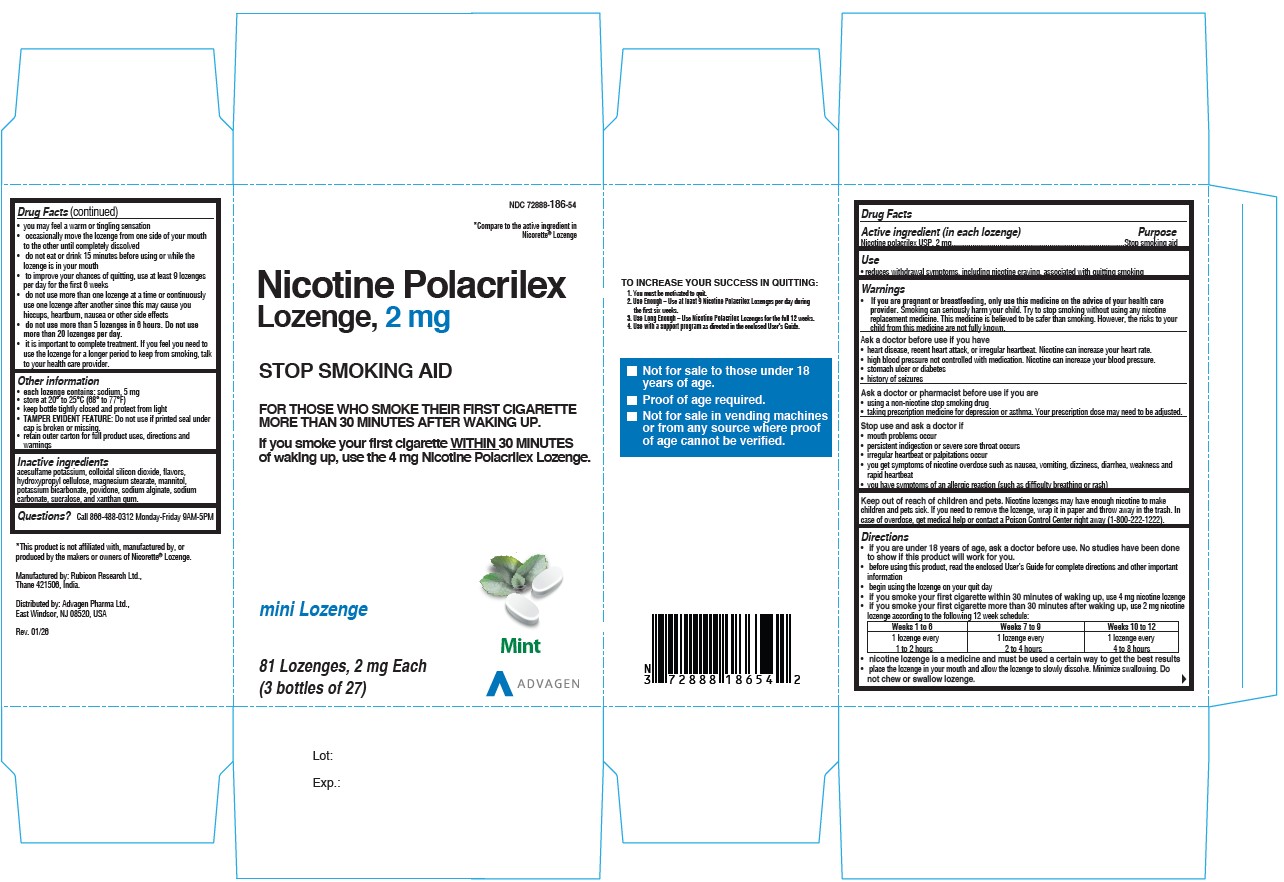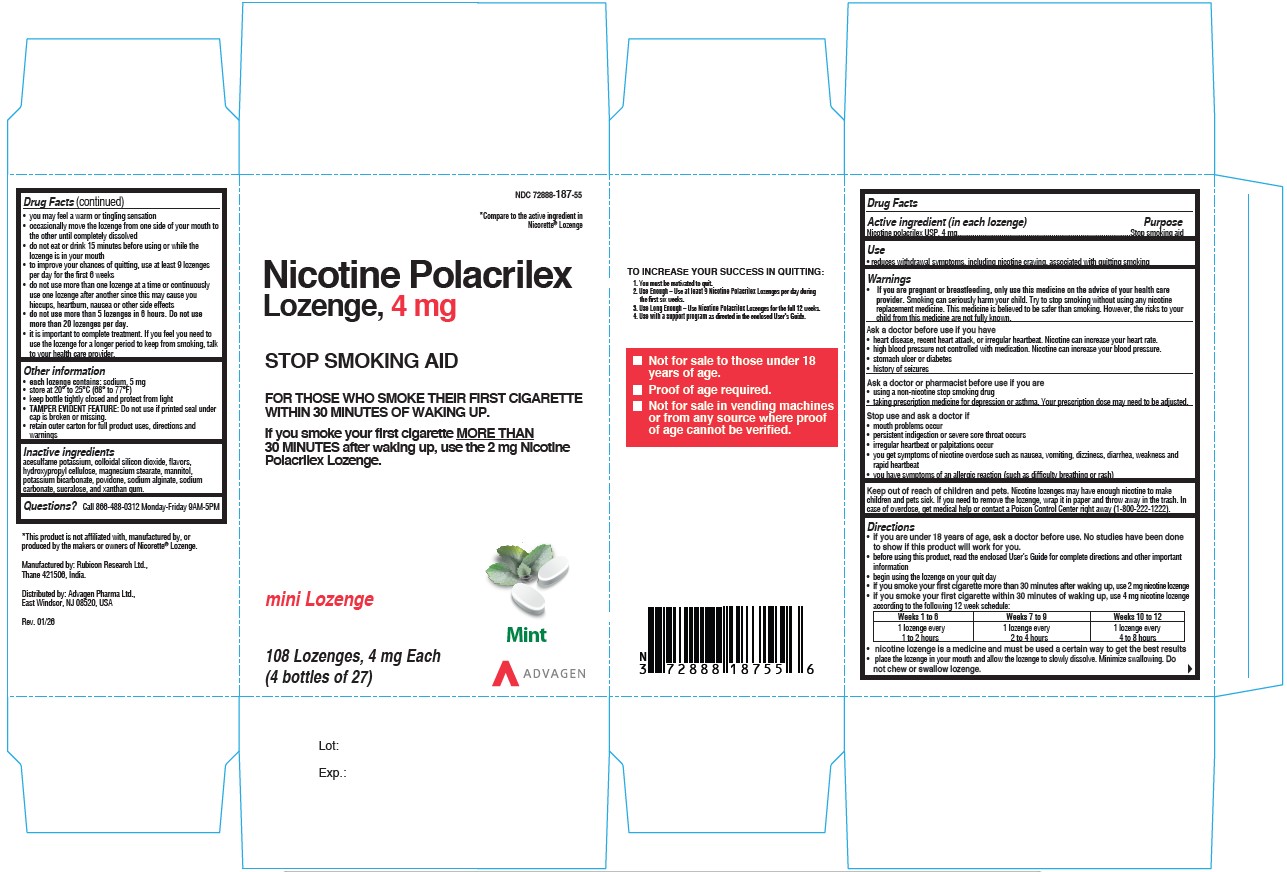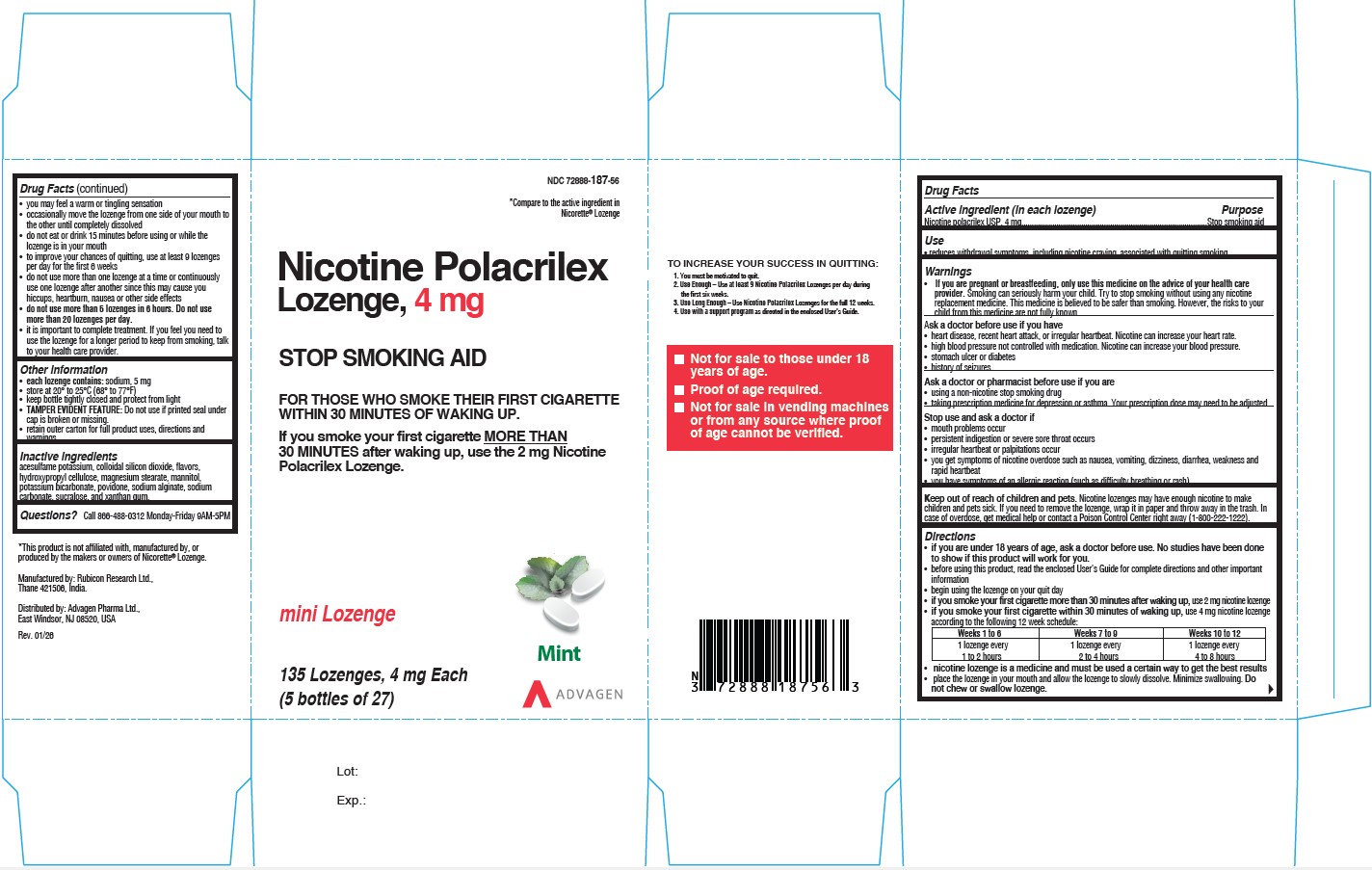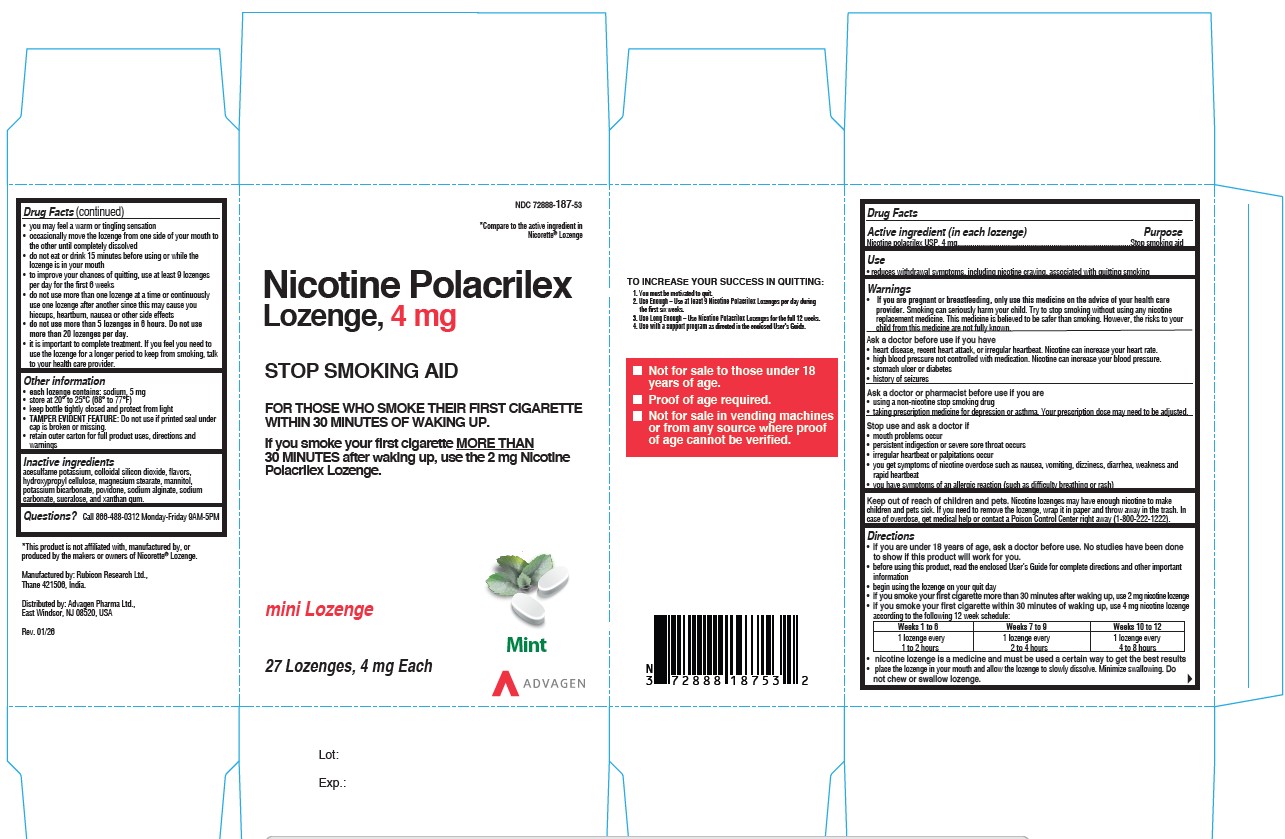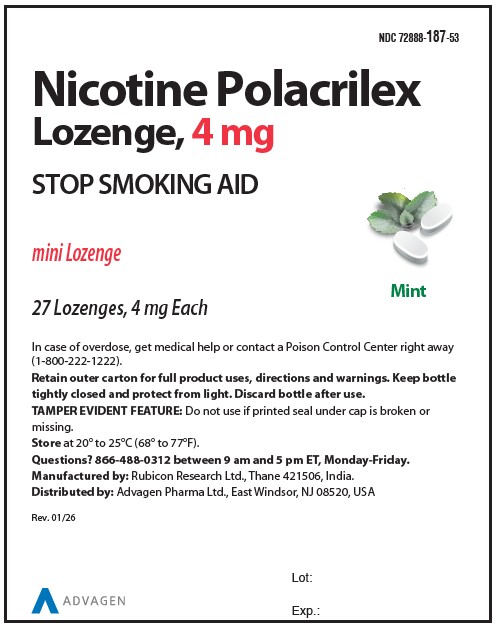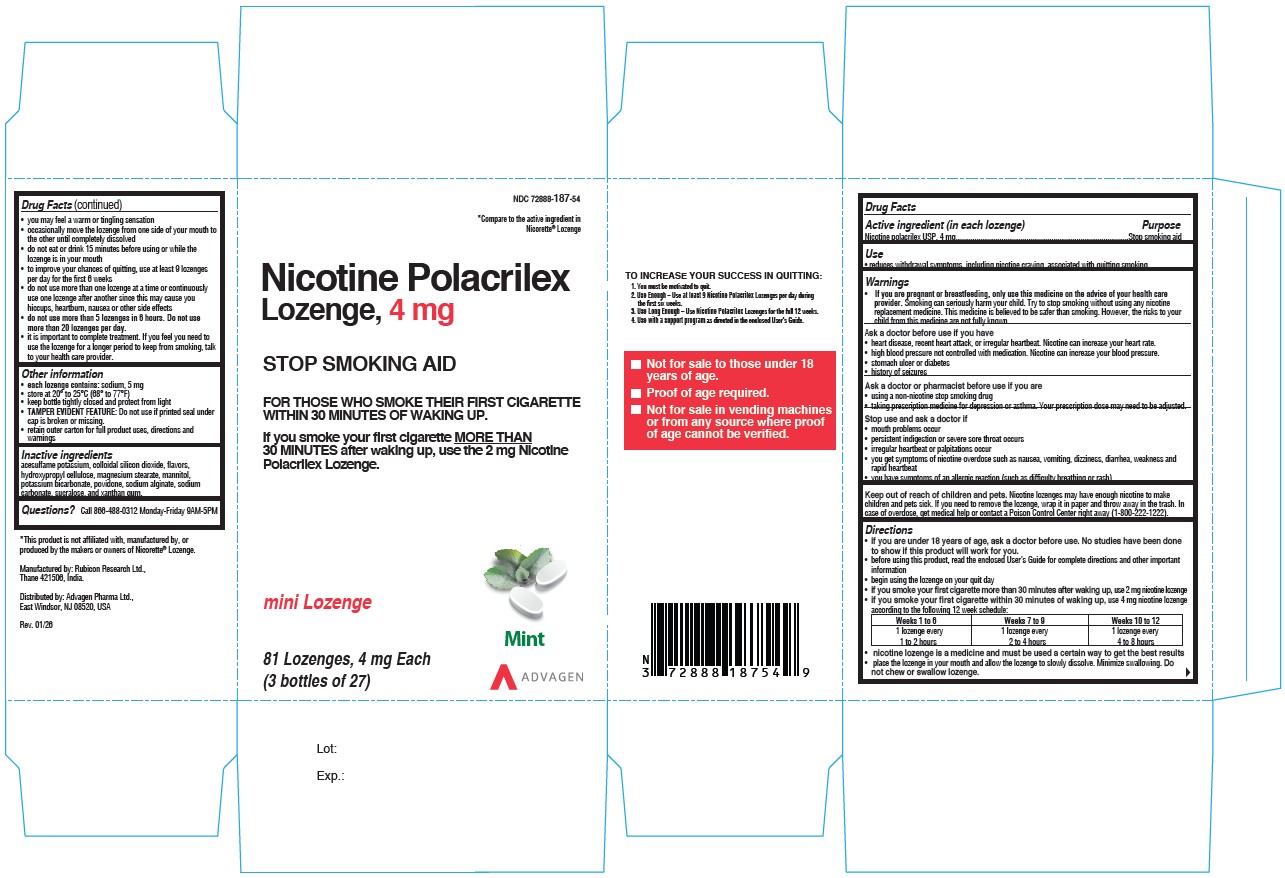 DRUG LABEL: Nicotine Mini
NDC: 72888-186 | Form: LOZENGE
Manufacturer: Advagen Pharma Limited
Category: otc | Type: HUMAN OTC DRUG LABEL
Date: 20260114

ACTIVE INGREDIENTS: NICOTINE 2 mg/1 1
INACTIVE INGREDIENTS: ACESULFAME POTASSIUM; SILICON DIOXIDE; HYDROXYPROPYL CELLULOSE, UNSPECIFIED; MAGNESIUM STEARATE; MANNITOL; POTASSIUM BICARBONATE; POVIDONE; SODIUM ALGINATE; SODIUM CARBONATE; SUCRALOSE; XANTHAN GUM

Drugs Facts
Active ingredient (in each lozenge) Nicotine polacrilex 4 mg Nicotine polacrilex 2 mg
Purpose Stop smoking aid
Use reduces withdrawal symptoms, including nicotine craving, associated with quitting smoking
Warnings If you are pregnant or breast-feeding, only use this medicine on the advice of your health care provider. Smoking can seriously harm your child. Try to stop smoking without using any nicotine replacement medicine. This medicine is believed to be safer than smoking. However, the risks to your child from this medicine are not fully known.
Ask a doctor before use if you have heart disease, recent heart attack, or irregular heartbeat. Nicotine can increase your heart rate. high blood pressure not controlled with medication. Nicotine can increase your blood pressure. stomach ulcer or diabetes history of seizures
Ask a doctor or pharmacist before use if you are using a non-nicotine stop smoking drug taking prescription medicine for depression or asthma. Your prescription dose may need to be adjusted.
Stop use and ask a doctor if mouth problems occur persistent indigestion or severe sore throat occurs irregular heartbeat or palpitations occur you get symptoms of nicotine overdose such as nausea, vomiting, dizziness, diarrhea, weakness and rapid heartbeat you have symptoms of an allergic reaction (such as difficulty breathing or rash)
Keep out of reach of children and pets. Nicotine lozenges may have enough nicotine to make children and pets sick. If you need to remove the lozenge, wrap it in paper and throw away in the trash. In case of overdose, get medical help or contact a Poison Control Center right away.
Directions (4 mg lozenge)if you are under 18 years of age, ask a doctor before use. No studies have been done to show if this product will work for you.before using this product, read the enclosed User's Guide for complete directions and other important informationbegin using the lozenge on your quit dayif you smoke your first cigarette more than 30 minutes after waking up, use 2 mg nicotine lozengeif you smoke your first cigarette within 30 minutes of waking up,use 4 mg nicotine lozenge according to the following 12 week schedule:

Weeks 1 to 6 | Weeks 7 to 9 | Weeks 10 to 12
1 lozenge every 1 to 2 hours | 1 lozenge every 2 to 4 hours | 1 lozenge every 4 to 8 hours

nicotine lozenge is a medicine and must be used a certain way to get the best results place the lozenge in your mouth and allow the lozenge to slowly dissolve. Minimize swallowing. Do not chew or swallow lozenge. you may feel a warm or tingling sensation occasionally move the lozenge from one side of your mouth to the other until completely dissolved do not eat or drink 15 minutes before using or while the lozenge is in your mouth to improve your chances of quitting, use at least 9 lozenges per day for the first 6 weeks do not use more than one lozenge at a time or continuously use one lozenge after another since this may cause you hiccups, heartburn, nausea or other side effects do not use more than 5 lozenges in 6 hours. Do not use more than 20 lozenges per day. It is important to complete treatment. If you feel you need to use the lozenge for a longer period to keep from smoking, talk to your health care provider.
Directions (2 mg lozenge)if you are under 18 years of age, ask a doctor before use. No studies have been done to show if this product will work for you.before using this product, read the enclosed User's Guide for complete directions and other important informationbegin using the lozenge on your quit dayif you smoke your first cigarette within 30 minutes of waking up, use 4 mg nicotine lozengeif you smoke your first cigarette more than 30 minutes after waking up,use 2 mg nicotine lozenge according to the following 12 week schedule:

Weeks 1 to 6 | Weeks 7 to 9 | Weeks 10 to 12
1 lozenge every 1 to 2 hours | 1 lozenge every 2 to 4 hours | 1 lozenge every 4 to 8 hours

nicotine lozenge is a medicine and must be used a certain way to get the best results place the lozenge in your mouth and allow the lozenge to slowly dissolve. Minimize swallowing. Do not chew or swallow lozenge. you may feel a warm or tingling sensation occasionally move the lozenge from one side of your mouth to the other until completely dissolved do not eat or drink 15 minutes before using or while the lozenge is in your mouth to improve your chances of quitting, use at least 9 lozenges per day for the first 6 weeks do not use more than one lozenge at a time or continuously use one lozenge after another since this may cause you hiccups, heartburn, nausea or other side effects do not use more than 5 lozenges in 6 hours. Do not use more than 20 lozenges per day. It is important to complete treatment. If you feel you need to use the lozenge for a longer period to keep from smoking, talk to your health care provider.
Other information Each lozenge contains: sodium, 5 mg store at 20oto 25oC (68oto 77oF) keep bottle tightly closed and protect from light TAMPER EVIDENT FEATURE: Do not use if printed seal under cap is broken or missing. retain outer carton for full product uses, directions and warnings.
Inactive ingredients acesulfame potassium, colloidal silicon dioxide, flavors, hydroxypropyl cellulose, magnesium stearate, mannitol, potassium bicarbonate, povidone, sodium alginate, sodium carbonate, sucralose, and xanthan gum.
Questions or comments? Call 866-488-0312 Monday-Friday 9AM-5PM EST
Manufactured by Rubicon Research Ltd.,
Thane 421506, India.
Manufactured for Advagen Pharma Limited,
East Windsor, NJ 08520, USA
Rev: 01/2026

PACKAGE LABEL.PRINCIPAL DISPLAY PANEL

Nicotine Polacrilex Lozenge, 2 mg - NDC 72888-186-53 - 27s Container Label

Nicotine Polacrilex Lozenge, 2 mg - NDC 72888-186-53 - 27s Carton Label

Nicotine Polacrilex Lozenge, 2 mg - NDC 72888-186-54 - 81s Carton Label

Nicotine Polacrilex Lozenge, 2 mg - NDC 72888-186-55 - 108s Carton Label

Nicotine Polacrilex Lozenge, 2 mg - NDC 72888-186-56 - 135s Carton Label

PACKAGE LABEL

Nicotine Polacrilex Lozenge, 4 mg - NDC 72888-187-53 - 27s Container Label

Nicotine Polacrilex Lozenge, 4 mg - NDC 72888-187-53 - 27s Carton Label

Nicotine Polacrilex Lozenge, 4 mg - NDC 72888-187-54 - 81s Carton Label

Nicotine Polacrilex Lozenge, 4 mg - NDC 72888-187-55 - 108s Carton Label

Nicotine Polacrilex Lozenge, 4 mg - NDC 72888-187-56 - 135s Carton Label